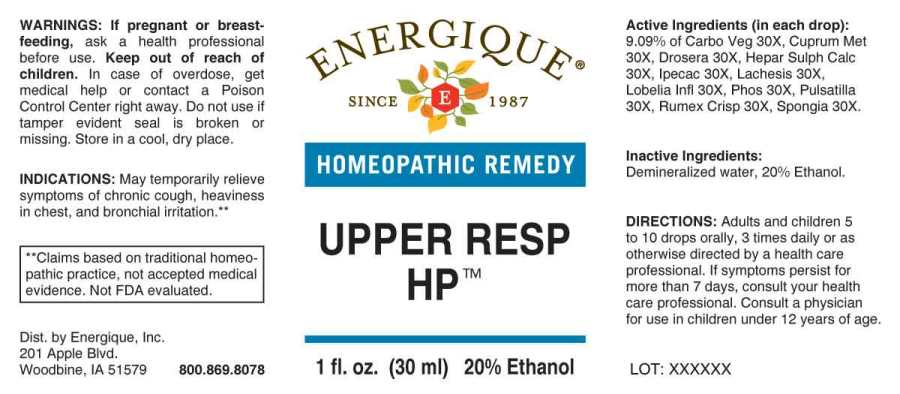 DRUG LABEL: Upper Resp HP
NDC: 44911-0595 | Form: LIQUID
Manufacturer: Energique, Inc.
Category: homeopathic | Type: HUMAN OTC DRUG LABEL
Date: 20241031

ACTIVE INGREDIENTS: ACTIVATED CHARCOAL 30 [hp_X]/1 mL; COPPER 30 [hp_X]/1 mL; DROSERA ROTUNDIFOLIA WHOLE 30 [hp_X]/1 mL; CALCIUM SULFIDE 30 [hp_X]/1 mL; IPECAC 30 [hp_X]/1 mL; LACHESIS MUTA VENOM 30 [hp_X]/1 mL; LOBELIA INFLATA WHOLE 30 [hp_X]/1 mL; PHOSPHORUS 30 [hp_X]/1 mL; PULSATILLA PRATENSIS WHOLE 30 [hp_X]/1 mL; RUMEX CRISPUS ROOT 30 [hp_X]/1 mL; SPONGIA OFFICINALIS SKELETON, ROASTED 30 [hp_X]/1 mL
INACTIVE INGREDIENTS: WATER; ALCOHOL

DRUG FACTS:

ACTIVE INGREDIENTS:

(in each drop): 9.09% of Carbo Vegetabilis 30X, Cuprum Metallicum 30X, Drosera (Rotundifolia) 30X, Hepar Sulphuris Calcareum 30X, Ipecacuanha 30X, Lachesis Mutus 30X, Lobelia Inflata 30X, Phosphorus 30X, Pulsatilla (Pratensis) 30X, Rumex Crispus 30X, Spongia Tosta 30X.

INDICATIONS:

May temporarily relieve symptoms of chronic cough, heaviness in chest, and bronchial irritation.**

**Claims based on traditional homeopathic practice, not accepted medical evidence. Not FDA evaluated.

WARNINGS:

If pregnant or breast-feeding, ask a health professional before use.

Keep out of reach of children. In case of overdose, get medical help or contact a Poison Control Center right away.

Do not use if tamper evident seal is broken or missing. Store in a cool, dry place.

Keep out of reach of children. In case of overdose, get medical help or contact a Poison Control Center right away.

DIRECTIONS:

Adults and children 5 to 10 drops orally, 3 times daily or as otherwise directed by a health care professional. If symptoms persist for more than 7 days, consult your health care professional. Consult a physician for use in children under 12 years of age.

INDICATIONS:

May temporarily relieve symptoms of chronic cough, heaviness in chest, and bronchial irritation.**

**Claims based on traditional homeopathic practice, not accepted medical evidence. Not FDA evaluated.

INACTIVE INGREDIENTS:

Demineralized water, 20% Ethanol.

QUESTIONS:

Dist. by Energique, Inc.

201 Apple Blvd

Woodbine, IA 51579 800-869-8078

PACKAGE LABEL DISPLAY:

ENERGIQUE

SINCE 1987

HOMEOPATHIC REMEDY

UPPER RESP HP

1 fl. oz. (30 ml)